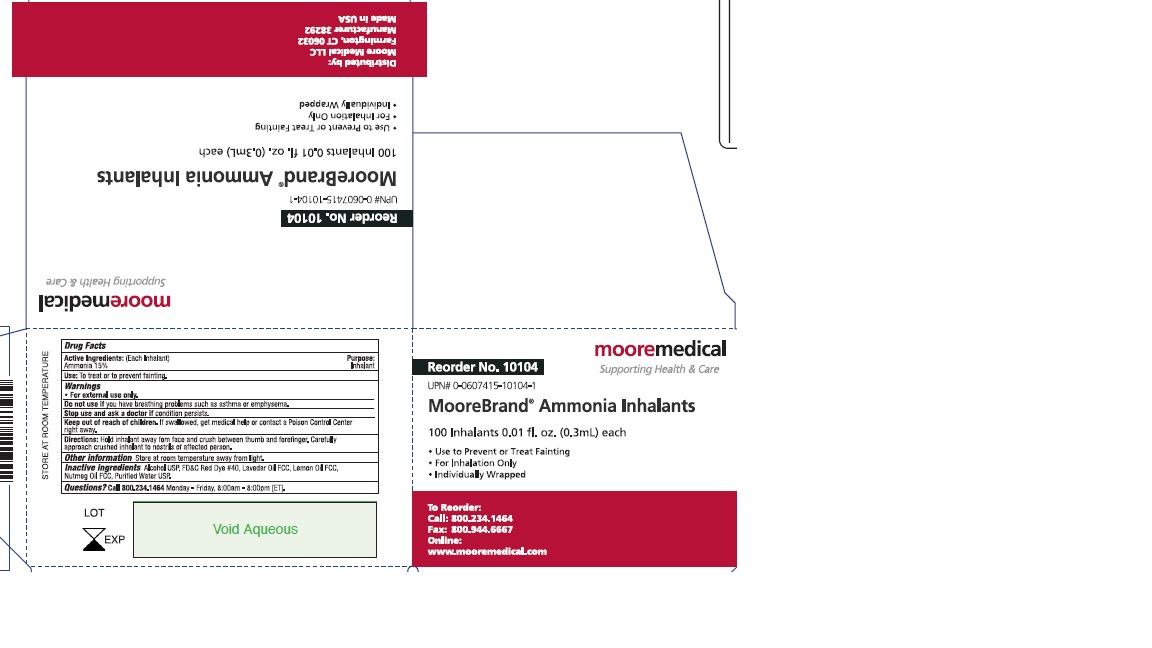 DRUG LABEL: Ammonia Inhalant
NDC: 73395-196 | Form: AEROSOL
Manufacturer: AmmoniaSport LLC
Category: otc | Type: HUMAN OTC DRUG LABEL
Date: 20200427

ACTIVE INGREDIENTS: AMMONIA 0.045 g/0.3 mL
INACTIVE INGREDIENTS: NUTMEG OIL; FD&C RED NO. 40; LAVENDER OIL; ALCOHOL; LEMON OIL; WATER

AmmoniaSport Ammonia Inhalants

Drug Facts

Active Ingredients: (Each Inhalant)
Ammonia 15%

Purpose
Inhalant

INDICATIONS AND USAGE

Uses: To treat or to prevent fainting.

Warnings
For external use only
Do not use if you have breathing problems such as asthma or emphysema.

Stop use and ask doctor if condition persists

Keep out of reach of children. If swallowed, get medical help or contact a Poison Control Center right away.

DOSAGE AND ADMINISTRATION

Directions: Hold inhalant away from face and crush between thumb and forefinger. Carefully approach crushed inhalant to nostrils of affected person.

Other Information: Store at room temperature away from light.

INACTIVE INGREDIENT

Inactive ingredients: Alcohol USP, FD&C Red Dye #40, Lavender Oil FCC, Lemon Oil FCC, Nutmeg Oil FCC, Purified Water USP.

QUESTIONS

Questions? Call 800-234-1464 Monday – Friday, 8:00am – 8:00pm [ET].

PACKAGE LABEL

Reorder No. 10104
Moore Medical
Supporting Health & Care
UPN# 0-0607415-10104-1
Moore Brand Ammonia Inhalants
100 Inhalants 0.01 fl. Oz. (0.3mL) each
Use to prevent fainting
For inhalation only
Individually wrapped